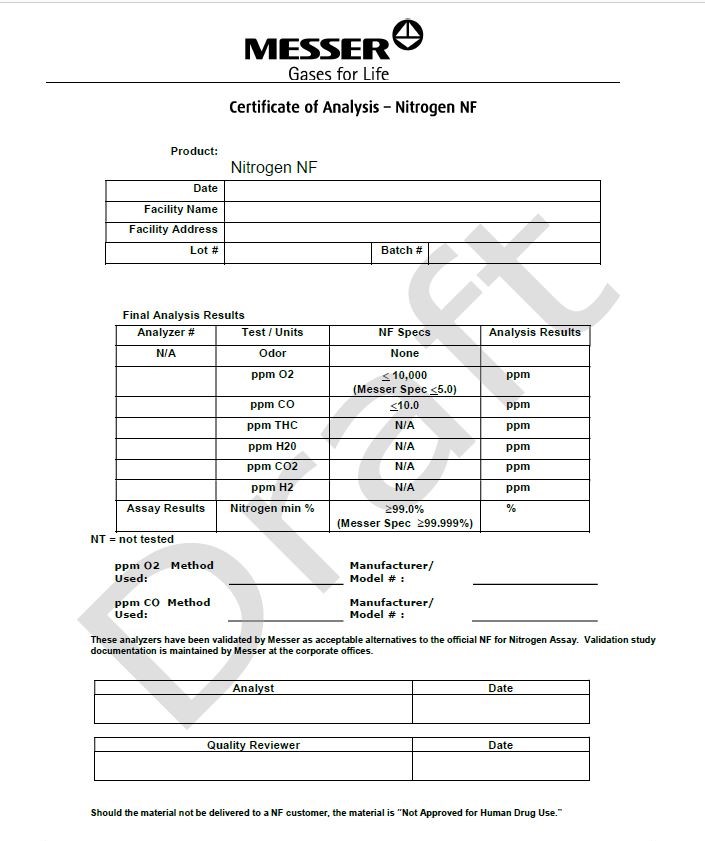 DRUG LABEL: Nitrogen 
NDC: 52003-016 | Form: GAS
Manufacturer: Messer Canada Inc.
Category: prescription | Type: HUMAN PRESCRIPTION DRUG LABEL
Date: 20241017

ACTIVE INGREDIENTS: Nitrogen 995 mL/1 L

Nitrogen NF Bulk Liquid

WARNINGS AND PRECAUTIONS SECTION

Should the material not be delivered to a NF customer, the material is “Not Approved for Human Drug Use.”

PACKAGE LABEL.PRINCIPAL DISPLAY PANEL

Messer
Gases for Life

Certicate of Analysis - Nitrogen NF

Product: Nitrogen NF

Date

Facility Name

Facility Address

Lot#

Batch #

Final Analysis Results

Analyzer # | Test/Units | NF Specs | Analysis Results
N/A | Odor | None
 | ppm O2 | < 10,000; (Messer Spec <5.0) | ppm
 | ppm CO | < 10.0 | ppm
 | ppm THC | N/A | ppm
 | ppm H2O | N/A | ppm
 | ppm CO2 | N/A | ppm
 | ppm H2 | N/A | ppm
Assay Results | Nitrogen min % | > 99.0%; (Messer Spec >99.999%) | %

NT= not tested

PPM O2 Method Used: __________________________ | Manufacturer/Model #: __________________________
PPM O2 Method Used: __________________________ | Manufacturer/Model #: __________________________

This analyzer has been validated by Messer as acceptable alternatives to the official NF for Nitrogen Assay. Validation study documentation is maintained by Messer at the corporate offices.

Analyst | Date

Quality Reviewer | Date

Should the material not be delivered to a NF customer, the material is “Not Approved for Human Drug Use.”